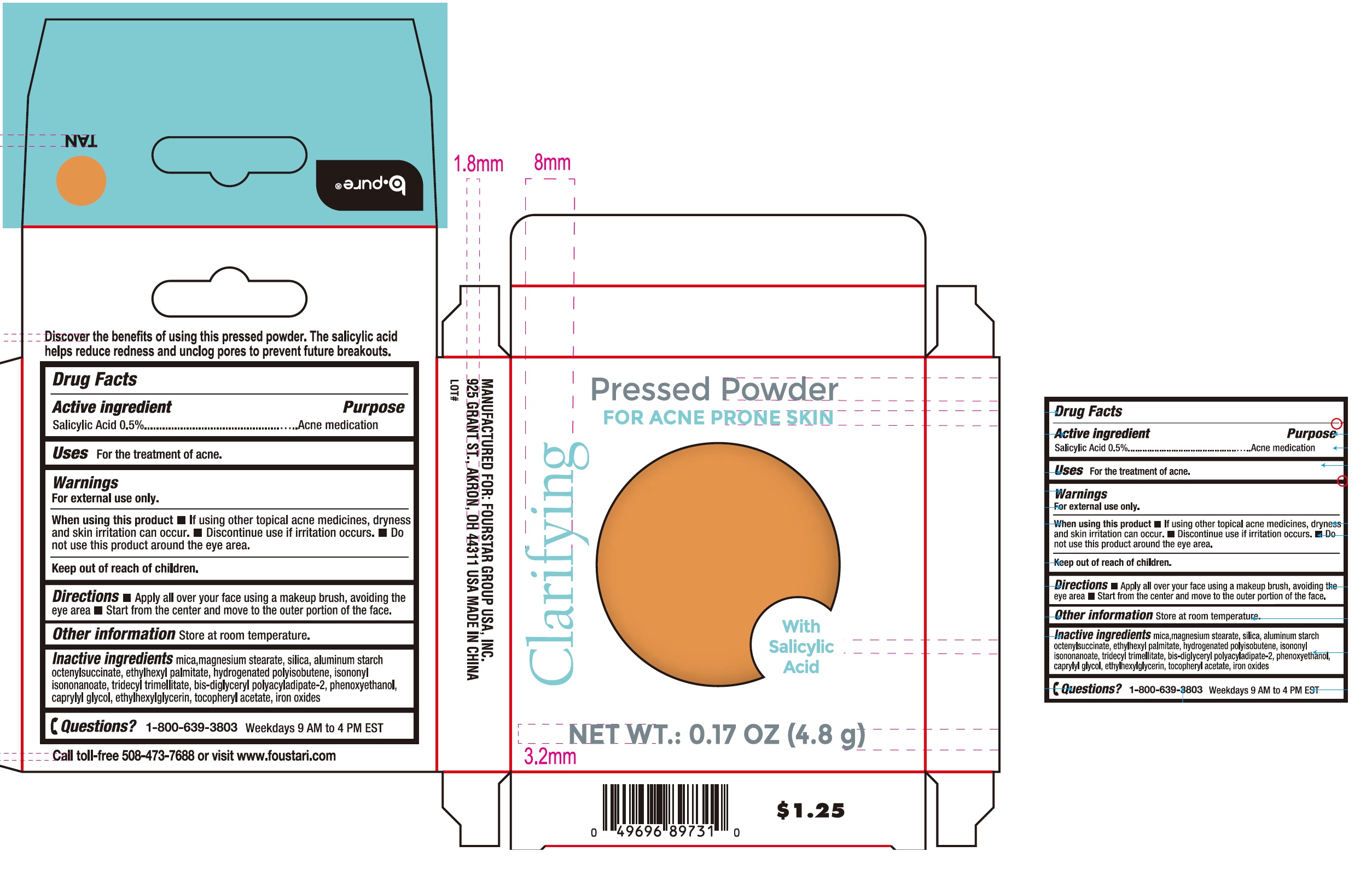 DRUG LABEL: b pure Pressed Powder for Acne Prone Skin Tan
NDC: 80684-111 | Form: POWDER
Manufacturer: Fourstar Group USA, Inc.
Category: otc | Type: HUMAN OTC DRUG LABEL
Date: 20240617

ACTIVE INGREDIENTS: SALICYLIC ACID 5 mg/1 g
INACTIVE INGREDIENTS: MICA; MAGNESIUM STEARATE; SILICON DIOXIDE; ALUMINUM STARCH OCTENYLSUCCINATE; ETHYLHEXYL PALMITATE; ISONONYL ISONONANOATE; TRIDECYL TRIMELLITATE; BIS-DIGLYCERYL POLYACYLADIPATE-2; PHENOXYETHANOL; CAPRYLYL GLYCOL; ETHYLHEXYLGLYCERIN; .ALPHA.-TOCOPHEROL ACETATE; FERRIC OXIDE RED

b.pure Pressed Powder for Acne Prone Skin, Tan

Active ingredient

Salicylic Acid 0.5%

Purpose

Acne medication

Uses

For the treatment of acne.

Warnings

For external use only.

When using this product

- If using other topical acne medicines, dryness and skin irritation can occur.
- Discontinue use if irritation occurs.
- Do not use this product around the eye area.

Directions

- Apply all over your face using a makeup brush, avoiding the eye area
- Start from the center and move to the outer portion of the face.

Other information

Store at room temperature.

Inactive ingredients

mica, magnesium stearate, silica, aluminum starch octenylsuccinate, ethylhexyl palmitate, hydrogenated polyisobutene, isononyl isononanoate, tridecyl trimellitate, bis-diglyceryl polyacyladipate-2, phenoxyethanol, caprylyl glycol, ethylhexylglycerin, tocopheryl acetate, iron oxides

Questions?

1-800-639-3803

Weekdays 9 AM to 4 PM EST